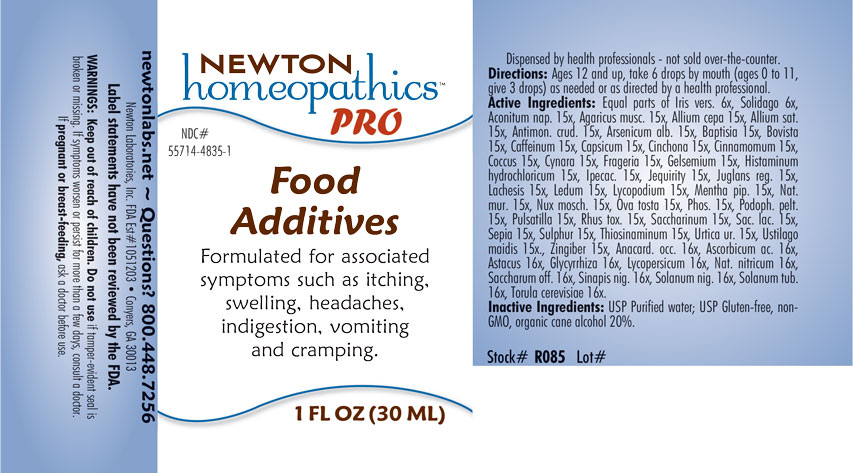 DRUG LABEL: Food Additives
NDC: 55714-4835 | Form: LIQUID
Manufacturer: Newton Laboratories, Inc.
Category: homeopathic | Type: HUMAN OTC DRUG LABEL
Date: 20201203

ACTIVE INGREDIENTS: BLACK MUSTARD SEED 16 [hp_X]/1 mL; SOLANUM NIGRUM WHOLE 16 [hp_X]/1 mL; ANACARDIUM OCCIDENTALE FRUIT 16 [hp_X]/1 mL; SOLANUM LYCOPERSICUM 16 [hp_X]/1 mL; SODIUM NITRITE 16 [hp_X]/1 mL; SODIUM CHLORIDE 15 [hp_X]/1 mL; ANEMONE PULSATILLA 15 [hp_X]/1 mL; TOXICODENDRON PUBESCENS LEAF 15 [hp_X]/1 mL; ALLYLTHIOUREA 15 [hp_X]/1 mL; IRIS VERSICOLOR ROOT 6 [hp_X]/1 mL; IPECAC 15 [hp_X]/1 mL; ACONITUM NAPELLUS 15 [hp_X]/1 mL; AMANITA MUSCARIA FRUITING BODY 15 [hp_X]/1 mL; ONION 15 [hp_X]/1 mL; GARLIC 15 [hp_X]/1 mL; PHOSPHORUS 15 [hp_X]/1 mL; SACCHARIN 15 [hp_X]/1 mL; ANTIMONY TRISULFIDE 15 [hp_X]/1 mL; ARSENIC TRIOXIDE 15 [hp_X]/1 mL; BAPTISIA TINCTORIA ROOT 15 [hp_X]/1 mL; LYCOPERDON UTRIFORME FRUITING BODY 15 [hp_X]/1 mL; CAFFEINE 15 [hp_X]/1 mL; CAPSICUM 15 [hp_X]/1 mL; CINCHONA OFFICINALIS BARK 15 [hp_X]/1 mL; CINNAMON 15 [hp_X]/1 mL; PROTORTONIA CACTI 15 [hp_X]/1 mL; CYNARA SCOLYMUS LEAF 15 [hp_X]/1 mL; ALPINE STRAWBERRY 15 [hp_X]/1 mL; GELSEMIUM SEMPERVIRENS ROOT 15 [hp_X]/1 mL; HISTAMINE DIHYDROCHLORIDE 15 [hp_X]/1 mL; SOLIDAGO VIRGAUREA FLOWERING TOP 6 [hp_X]/1 mL; URTICA URENS 15 [hp_X]/1 mL; GINGER 15 [hp_X]/1 mL; SUCROSE 16 [hp_X]/1 mL; MENTHA PIPERITA 15 [hp_X]/1 mL; ABRUS PRECATORIUS SEED 15 [hp_X]/1 mL; JUGLANS REGIA LEAF 15 [hp_X]/1 mL; USTILAGO MAYDIS 15 [hp_X]/1 mL; LACHESIS MUTA VENOM 15 [hp_X]/1 mL; NUTMEG 15 [hp_X]/1 mL; PODOPHYLLUM 15 [hp_X]/1 mL; SULFUR 15 [hp_X]/1 mL; ASTACUS ASTACUS 16 [hp_X]/1 mL; GLYCYRRHIZA GLABRA 16 [hp_X]/1 mL; SOLANUM TUBEROSUM 16 [hp_X]/1 mL; SACCHAROMYCES CEREVISIAE 16 [hp_X]/1 mL; LACTOSE, UNSPECIFIED FORM 15 [hp_X]/1 mL; SEPIA OFFICINALIS JUICE 15 [hp_X]/1 mL; EGG SHELL, COOKED 15 [hp_X]/1 mL; LYCOPODIUM CLAVATUM SPORE 15 [hp_X]/1 mL; RHODODENDRON TOMENTOSUM LEAFY TWIG 15 [hp_X]/1 mL; ASCORBIC ACID 16 [hp_X]/1 mL
INACTIVE INGREDIENTS: WATER; ALCOHOL

Food 4835L

INDICATIONS & USAGE SECTION

Formulated for associated symptoms such as itching, swelling, headaches, indigestiion, vomiting and cramping.

DOSAGE & ADMINISTRATION SECTION

Directions: Ages 12 and up, take 6 drops by mouth (ages 0 to 11, give 3 drops) as needed or directed by a health professional.

OTC - ACTIVE INGREDIENT SECTION

Equal parts of Iris versicolor 6x, Solidago virgaurea 6x, Aconitum napellus 15x, Agaricus muscarius 15x, Allium cepa 15x, Allium sativum 15x, Antimonium crudum 15x, Arsenicum album 15x, Baptisia tinctoria 15x, Bovista 15x, Caffeinum 15x, Capsicum annuum 15x, Cinchona officinalis 15x, Cinnamomum 15x, Coccus cacti 15x, Cynara scolymus 15x, Fragaria vesca 15x, Gelsemium sempervirens 15x, Histaminum hydrochloricum 15x, Ipecacuanha 15x, Jequerity 15x, Juglans regia 15x, Lachesis mutus 15x, Ledum palustre 15x, Lycopodium clavatum 15x, Mentha piperita 15x, Natrum muriaticum 15x, Nux moschata 15x, Ova tosta 15x, Phosphorus 15x, Podophyllum peltatum 15x, Pulsatilla 15x, Rhus toxicodendron 15x, Saccharinum 15x, Saccharum lactis 15x, Sepia 15x, Sulphur 15x, Thiosinaminum 15x, Urtica urens 15x, Ustilago maidis 15x, Zingiber officinale 15x, Anacardium occidentale 16x, Ascorbicum acidum 16x, Astacus fluviatilis 16x, Glycyrrhiza glabra 16x, Lycopersicum esculentum 16x, Natrum nitricum 16x, Saccharum officinale 16x, Sinapis nigra 16x, Solanum nigrum 16x, Solanum tuberosum 16x, Torula cerevisiae 16x.

OTC - PURPOSE SECTION

Formulated for associated symtoms such as itching, swelling, headaches, indigestion, vomiting and cramping.

INACTIVE INGREDIENT SECTION

Inactive Ingredients: USP Purified Water; USP Gluten-free, non-GMO, organic cane alcohol 20%.

QUESTIONS SECTION

newtonlabs.net - Questions? 800.448.7256

Newton Laboratories, Inc. FDA Est # 1051203 Conyers, GA 30013

WARNINGS SECTION

WARNINGS: Keep out of reach of children. Do not use if tamper-evident seal is broken or missing. If symptoms worsen or persist for more than a few days, consult a doctor. If pregnant or breast-feeding, ask a doctor before use.

OTC - PREGNANCY OR BREAST FEEDING SECTION

If pregnant or breast-feeding, ask a doctor before use.

OTC - KEEP OUT OF REACH OF CHILDREN SECTION

Keep out of reach of children.